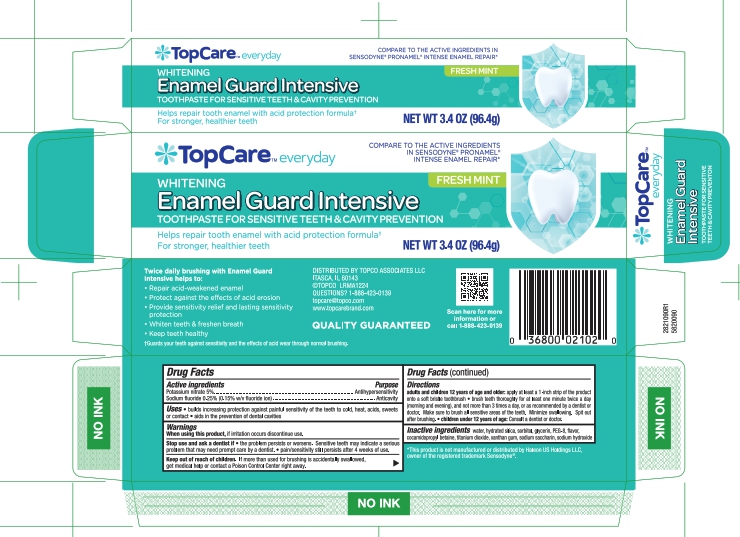 DRUG LABEL: Intensive Enamel Repair Whitening TP
NDC: 36800-362 | Form: PASTE, DENTIFRICE
Manufacturer: Topco Associates LLC
Category: otc | Type: HUMAN OTC DRUG LABEL
Date: 20250930

ACTIVE INGREDIENTS: POTASSIUM NITRATE 5 g/100 g; SODIUM FLUORIDE 0.15 g/100 g
INACTIVE INGREDIENTS: COCAMIDOPROPYL BETAINE; SORBITOL; GLYCERIN; PEG-8; XANTHAN GUM; TITANIUM DIOXIDE; WATER; SODIUM SACCHARIN; HYDRATED SILICA; SODIUM HYDROXIDE

5820090 TopCare Enamel Guard Intensive (8015074)

ACTIVE INGREDIENT

Potassium nitrate 5%

Sodium fluoride 0.25% (0.15% w/v fluoride ion)

PURPOSE

Antihypersensitivity

Anticavity

INDICATIONS AND USAGE

- builds increasing protection against painful sensitivity of the teeth to cold, heat, acids, sweets or contact
- aids in the prevention of dental cavities

WARNINGS

When using this product, if irritation occurs discontinue use.

Stop use and ask a dentist if

- the problem persists or worsens. Sensitive teeth may indicate a serious problem that may need prompt care by a dentist.
- pain/sensitivity still persists after 4 weeks of use.

Keep out of reach of children. If more than used for brushing is acidentally swallowed, get medical help or contact a Poison Control Center right away.

DOSAGE AND ADMINISTRATION

adults and children 12 years of age and older: apply at least a 1-inch strip of the product onto a soft bristle toothbrush

- brush teeth thoroughly for at least one minute twice a day (morning and evening), and not more than 3 times a day, or as recommended by a dentist or doctor. make sure to brush all sensitive areas of the teeth. Minimize swallowing. Spit out after brushing.
- children under 12 years of age: Consult a dentist or doctor.

INACTIVE INGREDIENT

water, hydrated silica, sorbitol, glycerin, PEG-8, flavor, cocamidopropyl betaine, titanium dioxide, xanthan gum, sodium saccharin, sodium hydroxide